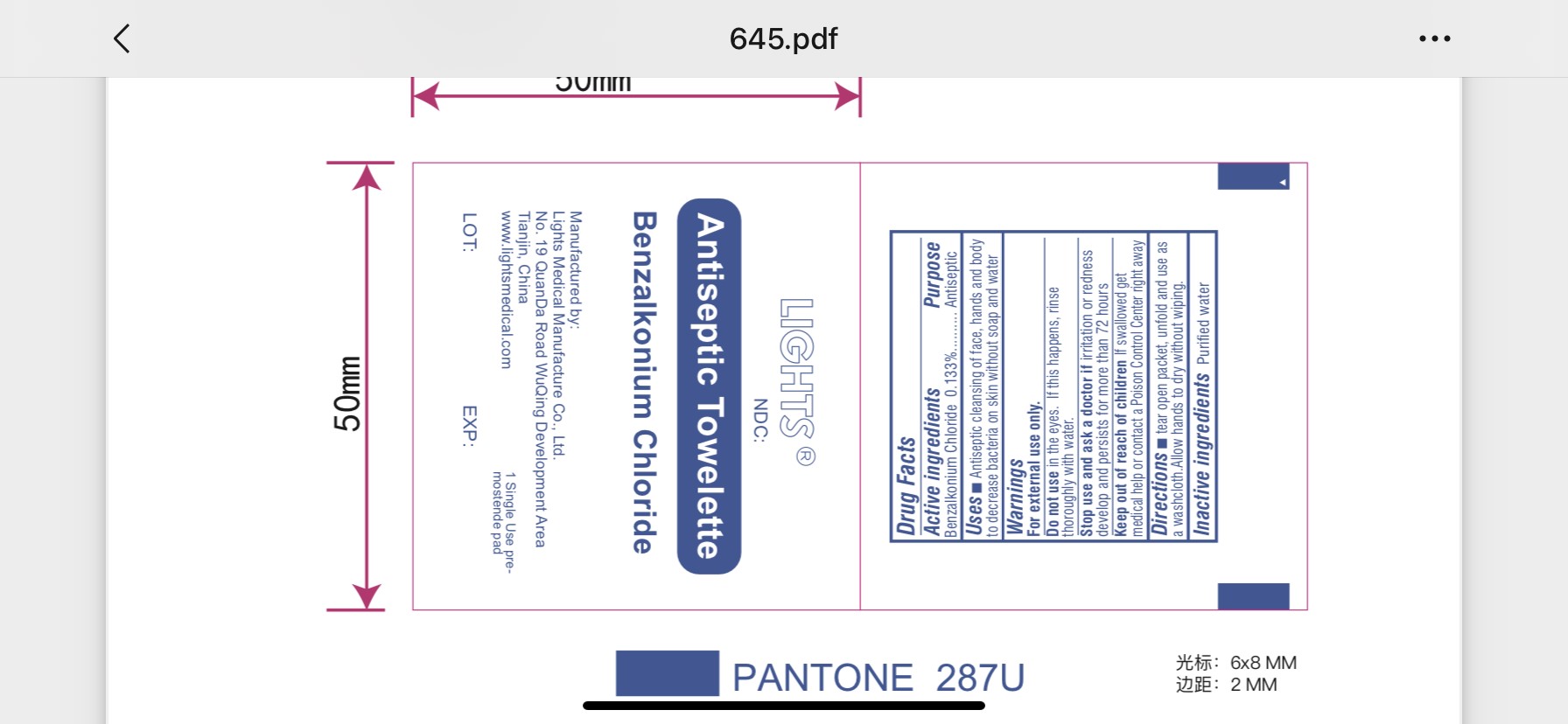 DRUG LABEL: LIGHTS Antiseptic Towelette
NDC: 61333-207 | Form: SOLUTION
Manufacturer: Lights Medical Manufacture Co., Ltd.
Category: otc | Type: HUMAN OTC DRUG LABEL
Date: 20220307

ACTIVE INGREDIENTS: BENZALKONIUM CHLORIDE 0.133 g/100 g
INACTIVE INGREDIENTS: WATER

61333-207

Active ingredient

benzalkonium chloride 0.133%

Purpose

Antiseptic

Uses

Antiseptic cleaning of face, hands and body to decrease bacteria on skin without soap and water.

Warnings

For external use only.

Do not use in the eyes. If this happens, rinse thoroughly with water

Stop use and ask a doctor if irritation or redness develops and persists for more than 72 hours

Keep out of reach of children
If swallowed, get medical help or contact a Poison Control Center right away.

Directions

Tear open packet, unfold and use as a washcloth. Allow hands to dry without wiping

INACTIVE INGREDIENT

Water